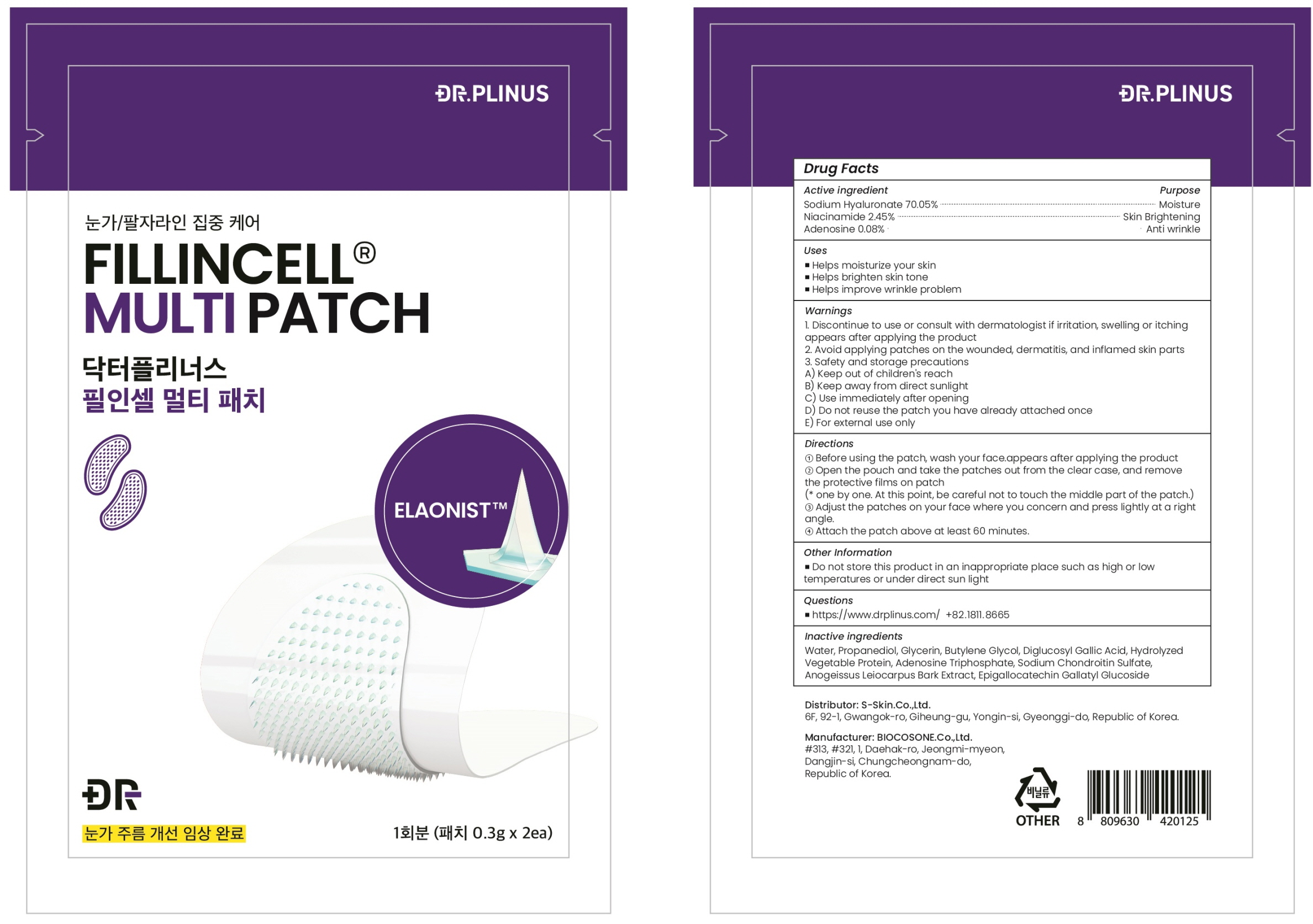 DRUG LABEL: DR.PLINUS FILLINCELL MULTI
NDC: 72630-020 | Form: PATCH
Manufacturer: S Skin Co., Ltd.
Category: otc | Type: HUMAN OTC DRUG LABEL
Date: 20221018

ACTIVE INGREDIENTS: HYALURONATE SODIUM 0.21 g/0.3 g; Niacinamide 0.007 g/0.3 g; Adenosine 0.0002 g/0.3 g
INACTIVE INGREDIENTS: Water; Propanediol; Glycerin

ACTIVE INGREDIENTS

Sodium Hyaluronate 70.05%
Niacinamide 2.45%
Adenosine 0.08%

INACTIVE INGREDIENTS

Water, Propanediol, Glycerin, Butylene Glycol, Diglucosyl Gallic Acid, Hydrolyzed Vegetable Protein, Adenosine Triphosphate, Sodium Chondroitin Sulfate, Anogeissus Leiocarpus Bark Extract, Epigallocatechin Gallatyl Glucoside

PURPOSE

Moisture
Skin Brightening
Anti wrinkle

WARNINGS

1. Discontinue to use or consult with dermatologist if irritation, swelling or itching appears after applying the product
2. Avoid applying patches on the wounded, dermatitis, and inflamed skin parts
3. Safety and storage precautions
A) Keep out of children's reach
B) Keep away from direct sunlight
C) Use immediately after opening
D) Do not reuse the patch you have already attached once
E) For external use only

KEEP OUT OF REACH OF CHILDREN

Keep out of children's reach

Uses

■ Helps moisturize your skin
■ Helps brighten skin tone
■ Helps improve wrinkle problem

Directions

① Before using the patch, wash your face.
② Open the pouch and take the patches out from the clear case, and remove the protective films on patch
(* one by one. At this point, be careful not to touch the middle part of the patch.)
③ Adjust the patches on your face where you concern and press lightly at a right angle.
④ Attach the patch above at least 60 minutes.

Other Information

■ Do not store this product in an inappropriate place such as high or low temperatures or under direct sun light

QUESTIONS

■ https://www.drplinus.com/ +82.1811.8665